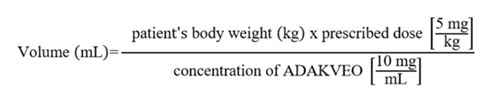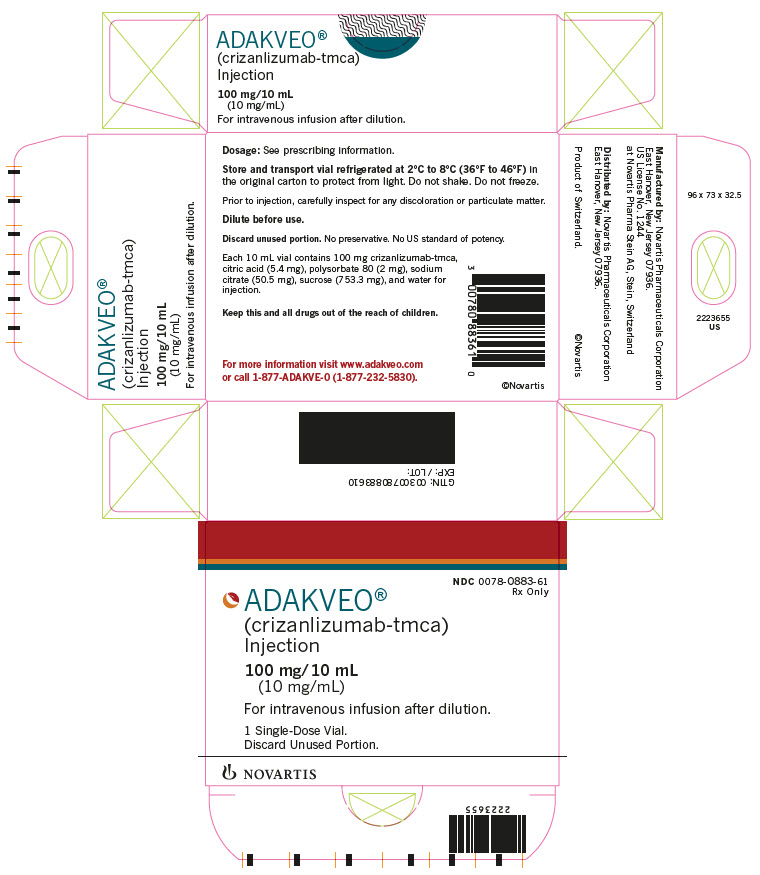 DRUG LABEL: ADAKVEO
NDC: 0078-0883 | Form: INJECTION
Manufacturer: Novartis Pharmaceuticals Corporation
Category: prescription | Type: HUMAN PRESCRIPTION DRUG LABEL
Date: 20250603

ACTIVE INGREDIENTS: CRIZANLIZUMAB 10 mg/1 mL
INACTIVE INGREDIENTS: SUCROSE 75.33 mg/1 mL; SODIUM CITRATE 5.053 mg/1 mL; CITRIC ACID MONOHYDRATE 0.54 mg/1 mL; POLYSORBATE 80 0.200 mg/1 mL; WATER

HIGHLIGHTS OF PRESCRIBING INFORMATION

These highlights do not include all the information needed to use ADAKVEO safely and effectively. See full prescribing information for ADAKVEO.
ADAKVEO® (crizanlizumab-tmca) injection, for intravenous use
Initial U.S. Approval: 2019

RECENT MAJOR CHANGES

Dosage and Administration, Recommended Dosage (2.1) | 6/2024
Warnings and Precautions, Infusion-Related Reactions (5.1) | 6/2024

1 INDICATIONS AND USAGE

ADAKVEO is a selectin blocker indicated to reduce the frequency of vasoocclusive crises in adults and pediatric patients aged 16 years and older with sickle cell disease.

2 DOSAGE AND ADMINISTRATION

Administer 5 mg/kg by intravenous infusion over a period of 30 minutes on Week 0, Week 2, and every 4 weeks thereafter. (2.1)

See Full Prescribing Information for instructions on preparation and administration. (2.2)

3 DOSAGE FORMS AND STRENGTHS

Injection: 100 mg/10 mL (10 mg/mL) solution in a single-dose vial.

4 CONTRAINDICATIONS

None.

5 WARNINGS AND PRECAUTIONS

- Infusion-Related Reactions: Monitor for and advise patients of signs and symptoms. Discontinue ADAKVEO infusion for severe reactions and manage medically. Temporarily interrupt or slow the rate of infusion for mild or moderate infusion-related reactions and initiate symptomatic treatment. Exercise caution with corticosteroids in patients with sickle cell disease unless clinically indicated (e.g., treatment of anaphylaxis). (5.1)
- Interference With Automated Platelet Counts (platelet clumping): Run test as soon as possible or use citrate tubes. (5.2)

6 ADVERSE REACTIONS

The most common adverse reactions (incidence ≥ 10%) were headache, arthralgia, nausea, back pain, fatigue, abdominal pain, pyrexia, diarrhea, vomiting, and oropharyngeal pain. (6.1)

To report SUSPECTED ADVERSE REACTIONS, contact Novartis Pharmaceuticals Corporation at 1-888-669-6682 or FDA at 1-800-FDA-1088 or www.fda.gov/medwatch.

8 USE IN SPECIFIC POPULATIONS

Pregnancy: May cause fetal harm. (8.1)

FULL PRESCRIBING INFORMATION

1 INDICATIONS AND USAGE

ADAKVEO® is indicated to reduce the frequency of vaso-occlusive crises (VOCs) in adults and pediatric patients aged 16 years and older with sickle cell disease.

2 DOSAGE AND ADMINISTRATION

2.1 Recommended Dosage

Administer ADAKVEO 5 mg/kg by intravenous infusion over a period of 30 minutes at Week 0, Week 2, and every 4 weeks thereafter.

If a dose is missed, administer ADAKVEO as soon as possible.

If ADAKVEO is administered within 2 weeks after the missed dose, continue dosing according to the patient's original schedule.

If ADAKVEO is administered more than 2 weeks after the missed dose, continue dosing every 4 weeks thereafter.

Physicians should reevaluate the treatment at least yearly, to assess individual patient’s response to treatment and consider discontinuing therapy with ADAKVEO if no perceived benefit is achieved.

ADAKVEO may be given with or without hydroxyurea.

2.2 Preparation and Administration

ADAKVEO should be prepared and administered by a healthcare professional.

Preparation

- Use aseptic technique to prepare the solution for infusion.
- Calculate the dose (mg) and the total volume (mL) of ADAKVEO solution required, and the number of ADAKVEO vials needed based on the patient’s actual body weight.
  - Prepare 5 mg of ADAKVEO per kg of actual body weight.
- Calculate the volume of ADAKVEO to be used according to the following equation:

Dilution

Dilute ADAKVEO in 0.9% Sodium Chloride Injection or 5% Dextrose Injection to a total volume of 100 mL for intravenous infusion as follows:

1. Obtain the number of vials required. One vial is needed for every 10 mL of ADAKVEO.
2. Bring vials to room temperature for a maximum of 4 hours prior to the start of preparation (piercing the first vial).
3. Visually inspect the vials.
  - Parenteral drug products should be inspected visually for particulate matter and discoloration prior to administration, whenever solution and container permit.
  - ADAKVEO is clear to opalescent, colorless or may have a slightly brownish-yellow tint.
  - Do not use if particles are present in the solution.
4. Obtain a 100 mL 0.9% Sodium Chloride Injection or 5% Dextrose Injection infusion bag/container.
  - Infusion bags/containers must be made of either polyvinyl chloride (PVC), polyethylene (PE), or polypropylene (PP).
5. Remove a volume of 0.9% Sodium Chloride Injection or 5% Dextrose Injection from the infusion bag/container that is equal to the required volume of ADAKVEO solution.
6. Withdraw the necessary amount of ADAKVEO solution and dilute by adding to the infusion bag/container containing 0.9% Sodium Chloride Injection or 5% Dextrose Injection.
  - The volume of ADAKVEO added to the infusion bag/container should not exceed 96 mL.
7. Gently invert the infusion bag to mix the diluted solution. DO NOT SHAKE.
8. Single-dose vials. Discard unused portion.

Storage Conditions of the Diluted Solution

Administer ADAKVEO diluted solution as soon as possible. If not administered immediately, store the prepared solution either:

- At room temperature up to 25°C (77°F) for no more than 4.5 hours from the start of the preparation (piercing the first vial) to the completion of infusion.
- Under refrigeration at 2°C to 8°C (36°F to 46°F) for no more than 24 hours, from the start of the time of the preparation (piercing the first vial) to the completion of infusion. This includes the storage of the diluted solution and the time to warm up to room temperature. Protect the diluted solution from light during storage under refrigeration.

Administration

- Administer ADAKVEO diluted solution by intravenous infusion over a period of 30 minutes through an intravenous line, which must contain a sterile, nonpyrogenic 0.2-micron inline filter.
- No incompatibilities have been observed between ADAKVEO and infusion sets composed of PVC, polyethylene (PE-lined PVC), polyurethane (PU), and in-line filter membranes composed of polyethersulfone (PES, neutral and positively charged), positively charged polyamide (PA), and polysulphone (PSU).
- Do not mix or coadminister with other drugs through the same intravenous line.
- After administration of ADAKVEO, flush the line with at least 25 mL of 0.9% Sodium Chloride Injection or 5% Dextrose Injection.
- Dispose of any unused product or waste material in accordance with local requirements.

3 DOSAGE FORMS AND STRENGTHS

Injection: 100 mg/10 mL (10 mg/mL) as a clear to opalescent, colorless to slightly brownish-yellow solution in a single-dose vial.

4 CONTRAINDICATIONS

None.

5 WARNINGS AND PRECAUTIONS

5.1 Infusion-Related Reactions

In the SUSTAIN clinical trial, infusion-related reactions (IRRs) (defined as occurring during/within 24 hours of infusion) were observed in 2 (3%) patients treated with ADAKVEO 5 mg/kg. In the STAND clinical trial, IRRs were observed in 6 (7%) patients treated with ADAKVEO 5 mg/kg.

IRRs presented most frequently as pain, nausea, vomiting, fatigue, dizziness, pruritis, diarrhea, and pyrexia. Some IRRs have required hospitalizations. The majority of these IRRs occurred during the first and second infusions.

Monitor for and advise patients to report signs and symptoms of IRRs. Discontinue ADAKVEO infusion for severe IRRs and institute appropriate medical care. Consider permanent discontinuation of ADAKVEO treatment in case of severe IRRs. Manage mild to moderate infusion-related reactions with temporary interruption of infusion, slowing the rate of infusion, symptomatic treatment (e.g., acetaminophen, non-steroidal anti-inflammatory drugs (NSAIDS), opioids, antihistamines, intravenous fluids, and/or oxygen therapy). For subsequent infusions, consider premedication and/or infusion rate reduction.

Exercise caution with corticosteroids in patients with sickle cell disease unless clinically indicated (e.g., treatment of anaphylaxis). Use of corticosteroids may increase the risk of complications such as acute chest syndrome and fat embolism.

Infusion-Related Reactions and Vaso-occlusive Crises

Infusion-related reactions are sometimes indistinguishable from vaso-occlusive crisis (VOC) events. IRRs and VOCs may occur concomitantly and/or VOCs may occur as a consequence of an IRR.

5.2 Laboratory Test Interference

Interference with automated platelet counts (platelet clumping) has been observed following administration of ADAKVEO, in particular, when blood samples were collected in tubes containing ethylenediaminetetraacetic acid (EDTA). Mitigation strategies are recommended [see Drug Interactions (7.1)].

6 ADVERSE REACTIONS

The following clinically significant adverse reactions are described elsewhere in the labeling:

- Infusion-related reactions [see Warnings and Precautions (5.1)]

6.1 Clinical Trials Experience

Because clinical trials are conducted under widely varying conditions, adverse reaction rates observed in the clinical trials of a drug cannot be directly compared to rates in the clinical trials of another drug and may not reflect the rates observed in practice.

Sickle Cell Disease

SUSTAIN Trial

The safety of ADAKVEO was evaluated in the SUSTAIN trial [see Clinical Studies (14.1)]. Eligible patients were diagnosed with sickle cell disease (any genotype, including HbSS, HbSC, HbS beta^0-thalassemia, HbS beta^+-thalassemia, and others). Patients received ADAKVEO 5 mg/kg (N = 66) or 2.5 mg/kg (N = 64) or placebo (N = 62) administered by intravenous infusion on Week 0, Week 2, and every 4 weeks thereafter. The safety evaluation below is limited to the patients who received the recommended dose of 5 mg/kg.

Among the 66 patients that received the recommended dose (5 mg/kg), 83% were exposed for 6 months or longer and 61% were exposed for approximately one year; forty-two (64%) patients were treated with ADAKVEO in combination with hydroxyurea.

Serious adverse reactions were reported in 2 patients (3%) treated with ADAKVEO 5 mg/kg; both reactions were pyrexia.

Two deaths (3%) occurred in the ADAKVEO 5 mg/kg treatment group. None of the deaths were considered to be related to ADAKVEO.

The most common adverse reactions (≥ 10%) were arthralgia, nausea, back pain, abdominal pain, pyrexia, and diarrhea.

Table 1 summarizes the adverse reactions in the SUSTAIN trial.

Table 1: Adverse Reactions (≥ 10%) in Patients Receiving ADAKVEO With a Difference Between Arms of > 3% Compared to Placebo in SUSTAIN
 | ADAKVEO 5 mg/kg N = 66 % |  | Placebo N = 62 %
Adverse Reactions | All Grades % | Grade ≥ 3 % | All Grades % | Grade ≥ 3 %
Arthralgia | 18 | 2 | 8 | 2
Nausea | 18 | 0 | 11 | 2
Back pain | 15 | 0 | 11 | 0
Abdominal paina | 12 | 0 | 5 | 0
Pyrexia | 11 | 12 | 7 | 0
Diarrhea | 11 | 0 | 3 | 2
aAbdominal pain: abdominal pain, upper abdominal pain, lower abdominal pain, and abdominal tenderness.

Clinically relevant adverse reactions (all Grades) that were reported in less than 10% of patients treated with ADAKVEO included: oropharyngeal pain, vomiting, pruritus (pruritus and vulvovaginal pruritus), musculoskeletal chest pain, myalgia, infusion-site reaction (infusion-site extravasation, infusion-site pain, and infusion-site swelling), and infusion-related reaction.

STAND Trial

The safety of ADAKVEO was also evaluated in the STAND trial [see Clinical Studies (14.1)]. Eligible patients were diagnosed with sickle cell disease (any genotype, including HbSS, HbSC, HbS beta^0-thalassemia, HbS beta^+-thalassemia, and others). Patients received ADAKVEO 5 mg/kg (N = 84) or 7.5 mg/kg (N = 83) or placebo (N = 85) administered by intravenous infusion on Week 0, Week 2, and every 4 weeks thereafter. The safety evaluation below is limited to the patients who received the recommended dose of 5 mg/kg.

Among the 84 patients that received the recommended dose (5 mg/kg), 93% were exposed for approximately 6 months or longer and 88% were exposed for approximately one year; sixty-two (74%) patients were treated with ADAKVEO in combination with hydroxyurea.

Serious adverse reactions were reported in 2 patients (2%) treated with ADAKVEO 5 mg/kg and this reaction was pain. The most common adverse reactions (≥ 10%) were headache, nausea, fatigue, vomiting, and oropharyngeal pain.

Table 2: Adverse Reactions (≥ 10%) in Patients Receiving ADAKVEO With a Difference Between Arms of > 3% Compared to Placebo in STAND
 | ADAKVEO 5 mg/kg N = 84 % |  | Placebo N = 85 %
Adverse Reactions | All Grades % | Grade ≥ 3 % | All Grades % | Grade ≥ 3 %
Headache | 25 | 1 | 19 | 0
Nausea | 17 | 0 | 9 | 0
Fatiguea | 13 | 0 | 8 | 0
Vomiting | 10 | 0 | 5 | 0
Oropharyngeal pain | 10 | 0 | 4 | 0
aFatigue includes asthenia and malaise.

Clinically relevant adverse reactions (all Grades) that were reported in less than 10% of patients treated with ADAKVEO or events having a difference of less than 3% between ADAKVEO treatment arms and placebo included: diarrhea, pruritus, dizziness, infusion-related reaction, infusion-site reaction.

7 DRUG INTERACTIONS

7.1 Laboratory Test Interference

Platelet Tests

ADAKVEO interferes with automated platelet counts (platelet clumping) in particular when blood samples are collected in tubes containing EDTA, which may lead to unevaluable or falsely decreased platelet counts. Run blood samples within 4 hours of blood collection or collect blood samples in tubes containing citrate. When needed, estimate platelet count via peripheral blood smear.

8 USE IN SPECIFIC POPULATIONS

8.1 Pregnancy

Risk Summary

Based on data from animal studies, ADAKVEO has the potential to cause fetal harm when administered to a pregnant woman. In an animal reproduction study, intravenous administration of crizanlizumab-tmca to pregnant cynomolgus monkeys from the onset of organogenesis through delivery resulted in a non-dose related increased fetal loss (abortions/stillbirths) at doses approximately 2.8 times the exposure at the recommended clinical dose at 5 mg/kg/dose once every 4 weeks (see Data).

There are insufficient human data on ADAKVEO use in pregnant women to evaluate for a drug-associated risk of major birth defects, miscarriage, or adverse maternal or fetal outcomes. Advise pregnant women of the potential risk to a fetus. ADAKVEO should only be used during pregnancy if the expected benefit to the patient justifies the potential risk to the fetus.

The estimated background risk of major birth defects and miscarriage for the indicated population is approximately 14% and up to 43%, respectively. All pregnancies have a background risk of birth defect, loss, or other adverse outcomes.

Clinical Considerations

Disease-Associated Maternal and/or Embryo/Fetal Risk

Women with sickle cell disease have an increased risk of adverse pregnancy outcomes for the mother and the fetus. Pregnant women are at greater risk for VOCs, pre-eclampsia, eclampsia, and maternal mortality. For the fetus, there is an increased risk for intrauterine growth restriction, preterm delivery, low birth weight, and perinatal mortality.

Data

Animal Data

In an enhanced pre- and postnatal development study in cynomolgus monkeys, pregnant animals received intravenous doses of crizanlizumab-tmca at 10 and 50 mg/kg once every 2 weeks during the period of onset of organogenesis through delivery. No maternal toxicity was observed. Maternal exposures at doses of 10 and 50 mg/kg were between 2.8 and 16 times, respectively, the human clinical exposure based on area under the curve (AUC) in patients with sickle cell disease at 5 mg/kg/dose once every 4 weeks. There was an increase in fetal loss (abortions or still births) at both crizanlizumab-tmca doses which was higher in the third trimester.

There were no effects on infant growth and development through 6-months postpartum that were attributable to crizanlizumab-tmca.

Measurable crizanlizumab-tmca serum concentrations were observed in the infant monkeys at postnatal Day 28, confirming that crizanlizumab crosses the placental barrier.

8.2 Lactation

Risk Summary

There is no data on the presence of crizanlizumab-tmca in human or animal milk, the effects on the breastfed child, or the effects on milk production. Maternal IgG is known to be present in human milk. The effects of local gastrointestinal exposure and limited systemic exposure in the breastfed child to crizanlizumab-tmca are unknown.

The developmental and health benefits of breast-feeding should be considered along with the mother’s clinical need for ADAKVEO and any potential adverse effects on the breastfed child from ADAKVEO or from the underlying maternal condition.

8.4 Pediatric Use

The safety and effectiveness of ADAKVEO for sickle cell disease have been established in pediatric patients aged 16 years and older. Use of ADAKVEO for sickle cell disease is supported by evidence from adequate and well-controlled studies in adults and pediatric patients (SUSTAIN trial). The SUSTAIN trial enrolled one pediatric patient treated with ADAKVEO 5 mg/kg aged 16 years old [see Adverse Reactions (6.1), Clinical Pharmacology (12.3), Clinical Studies (14)].

The safety and efficacy of ADAKVEO in pediatric patients below the age of 16 years have not been established.

8.5 Geriatric Use

There were no ADAKVEO-treated patients 65 years of age and older in the clinical studies for sickle cell disease [see Clinical Studies (14)]. Clinical studies of ADAKVEO did not include sufficient numbers of subjects aged 65 and over to determine whether they respond differently from younger subjects.

11 DESCRIPTION

Crizanlizumab-tmca is a P-selectin blocker humanized IgG2 kappa monoclonal antibody that binds to P-selectin. Crizanlizumab-tmca is produced using recombinant DNA technology in Chinese hamster ovary (CHO) cells. It is composed of 2 heavy chains, each containing 448 amino acids, and 2 light chains each containing 218 amino acids, with a theoretical molecular weight of approximately 146 kDa.

ADAKVEO (crizanlizumab-tmca) injection is supplied as a sterile, preservative-free, clear to opalescent, colorless to slightly brownish-yellow solution for dilution and subsequent administration by intravenous infusion. Each 10 mL vial contains 100 mg crizanlizumab-tmca, citric acid (5.4 mg), polysorbate 80 (2 mg), sodium citrate (50.5 mg), sucrose (753.3 mg), and water for injection with a pH of 6.

12 CLINICAL PHARMACOLOGY

12.1 Mechanism of Action

Crizanlizumab-tmca is a humanized IgG2 kappa monoclonal antibody that binds to P-selectin and blocks interactions with its ligands, including P-selectin glycoprotein ligand 1 (PSGL-1). Crizanlizumab can also dissociate preformed P-selectin/PSGL-1 complex.

Binding P-selectin on the surface of the activated endothelium and platelets blocks interactions between endothelial cells, platelets, red blood cells, and leukocytes.

12.2 Pharmacodynamics

ADAKVEO resulted in a dose-dependent P-selectin inhibition (measured ex vivo) in patients with sickle cell disease and healthy volunteers.

12.3 Pharmacokinetics

The pharmacokinetics of crizanlizumab-tmca were evaluated in healthy volunteers and patients with sickle cell disease. The mean crizanlizumab-tmca Cmax, AUClast, or AUCinf increased disproportionally over the dose range of 0.2 to 8 mg/kg (0.04 to 1.6 times the approved recommended dosage) in healthy volunteers. In healthy volunteers administered the 5 mg/kg dose, the mean [coefficient of variation (CV%)] crizanlizumab-tmca Cmax, AUClast, or AUCinf were 0.16 (15.3%) mg/mL, 33.6 (12.6%) mg*hr/mL and 34.6 (13.1%) mg*hr/mL, respectively.

Distribution

The mean (% CV) volume of distribution was 4.26 (25.1%) L after a single crizanlizumab-tmca 5 mg/kg intravenous infusion in healthy volunteers.

Elimination

The mean (% CV) terminal elimination half-life (t1/2) of crizanlizumab-tmca was 10.6 (20.5%) days and the mean clearance was 11.7 (16.2%) mL/hr at 5 mg/kg doses in healthy volunteers. The mean (% CV) elimination t1/2 of crizanlizumab-tmca was 11.4 (31.5%) days during dosing interval in patients with sickle cell disease.

Metabolism

Crizanlizumab-tmca is expected to be metabolized into small peptides by catabolic pathways.

Specific Populations

The effect of renal or hepatic impairment on the pharmacokinetics of crizanlizumab-tmca is unknown.

Drug Interaction Studies

Hydroxyurea had no clinically meaningful effect on crizanlizumab-tmca pharmacokinetics in patients in clinical studies.

12.6 Immunogenicity

The observed incidence of anti-drug antibodies is highly dependent on the sensitivity and specificity of the assay. Differences in assay methods preclude meaningful comparisons of the incidence of anti-drug antibodies in the studies described below with the incidence of anti-drug antibodies in other studies, including those of ADAKVEO or of other crizanlizumab products.

The immunogenicity of ADAKVEO was evaluated using a validated bridging immunoassay for the detection of binding anti-crizanlizumab-tmca antibodies. In a single arm, open label multiple dose study, 0 of the 45 patients with sickle cell disease treated with ADAKVEO 5 mg/kg tested positive for treatment-induced anti-crizanlizumab-tmca antibodies. In a single-dose study in healthy subjects, 1 of the 61 (1.6%) evaluable subjects tested positive for a treatment-induced anti-crizanlizumab-tmca antibodies. No treatment induced anti-crizanlizumab-tmca antibodies were detected (0 of 84 patients) in a Phase 3 study at 5 mg/kg over the 52 week time period (samples collected at baseline, Weeks 3, 15, 19, 27, and 51). Therefore, no significant effect on pharmacokinetics or pharmacodynamics has been observed or is expected.

13 NONCLINICAL TOXICOLOGY

13.1 Carcinogenesis, Mutagenesis, Impairment of Fertility

No carcinogenicity or genotoxicity studies have been conducted with crizanlizumab-tmca.

In the 26-week repeat-dose toxicity study, cynomolgus monkeys were administered crizanlizumab-tmca once every 4 weeks at doses up to 50 mg/kg (at least 13.1 times the human clinical exposure based on AUC in patients with sickle cell disease at 5 mg/kg once every 4 weeks). There were no adverse effects of crizanlizumab-tmca on male or female reproductive organs.

13.2 Animal Toxicology and/or Pharmacology

In the 26-week repeat-dose toxicity study, administration of crizanlizumab-tmca in cynomolgus monkeys at dose levels up to 50 mg/kg/dose once every 4 weeks resulted in inflammation of the vessels in multiple tissues in 2 out of 10 animals.

14 CLINICAL STUDIES

SUSTAIN

The efficacy of ADAKVEO was evaluated in patients with sickle cell disease in SUSTAIN [NCT01895361], a 52-week, randomized, multicenter, placebo-controlled, double-blind study. A total of 198 patients with sickle cell disease, any genotype (HbSS, HbSC, HbS/beta^0-thalassemia, HbS/beta^+-thalassemia, and others), and a history of 2-10 VOCs in the previous 12 months were eligible for inclusion. Patients were randomized 1:1:1 to ADAKVEO 5 mg/kg (N = 67), ADAKVEO 2.5 mg/kg (N = 66), or placebo (N = 65) administered over a period of 30 minutes by intravenous infusion on Week 0, Week 2, and every 4 weeks thereafter for a treatment duration of 52 weeks. Randomization was stratified by patients already receiving hydroxyurea (Y/N) and by the number of VOCs in the previous 12 months (2 to 4, 5 to 10).

Patients received ADAKVEO (with or without hydroxyurea) and were allowed to receive occasional transfusions and pain medications [i.e., acetaminophen, NSAIDs, and opioids] on an as needed basis.

Patients recruited in the study had complications associated with sickle cell disease and other comorbidities, including a history of acute chest syndrome (18%); pulmonary hypertension (8%); priapism (7%); psychiatric manifestations (25%), including depression and anxiety; hypertension (17%); cholelithiasis (17%). Demographic and other baseline characteristics were similar among the treatment groups (see Table 3).

Table 3: Demographics and Baseline Characteristics in SUSTAIN Study
 | ADAKVEO 5 mg/kg (N = 67) | Placebo (N = 65)
Age (years)
Median | 29 | 26
Range | 16, 63 | 16, 56
Gender, n (%)
Male | 32 (48%) | 27 (42%)
Female | 35 (52%) | 38 (59%)
Ethnicity, n (%)
Hispanic or Latino | 20 (30%) | 11 (17%)
Not Hispanic or Latino | 45 (67%) | 53 (82%)
Unknown | 2 (3%) | 1 (2%)
Race
Black or African American | 60 (90%) | 60 (92%)
White | 4 (6%) | 3 (5%)
Other | 3 (5%) | 2 (3%)
Sickle cell disease genotype, n (%)
HbSS | 47 (70%) | 47 (72%)
HbSC | 9 (13%) | 8 (12%)
HbS/beta^0 - thalassemia | 3 (5%) | 7 (11%)
HbS/beta^+ - thalassemia | 7 (10%) | 1 (2%)
Other | 1 (2%) | 2 (3%)
Hydroxyurea use, n (%)
Yes | 42 (63%) | 40 (62%)
No | 25 (37%) | 25 (39%)
Number of VOCs in previous 12 months, n (%)
2 to 4 | 42 (63%) | 41 (63%)
5 to 10 | 25 (37%) | 24 (37%)
Abbreviation: VOCs, vasoocclusive crises.

Efficacy was evaluated in the SUSTAIN study by the annual rate of VOCs leading to a healthcare visit. A VOC leading to a healthcare visit was defined as an acute episode of pain with no cause other than a vasoocclusive event that required a medical facility visit and treatment with oral or parenteral opioids, or parenteral NSAIDs. Acute chest syndrome, hepatic sequestration, splenic sequestration, and priapism (requiring a visit to a medical facility) were also considered VOCs.

Patients with sickle cell disease who received ADAKVEO 5 mg/kg had a lower median annual rate of VOC compared to patients who received placebo (1.63 vs. 2.98) which was statistically significant (p = 0.010). Reductions in the frequency of VOCs were observed among patients regardless of sickle cell disease genotype and/or hydroxyurea use.

Thirty-six percent (36%) of patients treated with ADAKVEO 5 mg/kg did not experience a VOC compared to 17% of placebo-treated patients. The median time to first VOC from randomization was 4.1 months in the ADAKVEO 5 mg/kg arm compared to 1.4 months in the placebo.

The main efficacy results of the pivotal study, SUSTAIN, are summarized in Table 4.

Table 4: Efficacy Results From SUSTAIN Trial in Sickle Cell Diseasea
Event | ADAKVEO, 5 mg/kgb (n = 67) | Placebob (n = 65) | Treatment Difference Estimatec
Annual rate of VOCsa | 1.63 | 2.98 | HL = -1.01, (-2.00, 0.00)
Annual rate of days hospitalized | 4 | 6.87
Abbreviations: HL, hodges-lehmann; VOCs, vasoocclusive crises.
aVOCs were as assessed by an independent review committee.
bStandard median.
cHL median difference [95% confidence interval (CI)].

STAND

The efficacy of two doses of ADAKVEO, with or without HU/HC, was evaluated, but not established, in the STAND trial [NCT03814746], a randomized, placebo-controlled, double-blind, multicenter clinical study in adolescent and adult sickle cell disease patients with a history of VOCs. The efficacy results of STAND study are summarized in Table 6 below.

In this study, VOC was defined as a pain crisis (acute onset of pain for which there is no other medically determined explanation other than vaso-occlusion) which requires therapy with oral or parenteral opioids or parenteral NSAID. Acute chest syndrome (ACS), priapism and hepatic or splenic sequestration were considered VOCs in this study.

A total of 252 sickle cell disease patients were randomized to the study, 85 in placebo arm, 84 in ADAKVEO 5 mg/kg arm and 83 in ADAKVEO 7.5 mg/kg arm. The 7.5 mg/kg ADAKVEO dose is not approved and is not recommended for use. Demographic and other baseline characteristics were similar among the treatment groups (see Table 5).

Table 5: Demographics and Baseline Characteristics in STAND Study
 | ADAKVEO 5 mg/kg (N = 84) | Placebo (N = 85)
Age (years)
Median | 24 | 25
Range | 12, 64 | 12, 68
Gender, n (%)
Female | 45 (54%) | 49 (58%)
Male | 39 (46%) | 36 (42%)
Race, n (%)
Black or African American | 46 (55%) | 43 (51%)
White | 27 (32%) | 26 (31%)
Asian | 6 (7%) | 6 (7%)
Other | 5 (6%) | 10 (12%)
Genotype, n (%)
HbSS | 58 (69%) | 58 (68%)
HbSC | 11 (13%) | 12 (14%)
HbS/beta^+ - thalassemia | 8 (10%) | 8 (9%)
HbS/beta^0 - thalassemia | 5 (6%) | 6 (7%)
Other | 2 (2%) | 1 (1%)
Ethnicity, n (%)
Not Hispanic or Latino | 54 (64%) | 57 (67%)
Hispanic or Latino | 22 (26%) | 18 (21%)
Other (not reported/unknown) | 8 (10%) | 10 (12%)
Hydroxyurea use, n (%)
Yes | 62 (74%) | 61 (72%)
No | 20 (24%) | 23 (27%)
Missing | 2 (2%) | 1 (1%)
Number of VOC leading to healthcare visit in the last 12 months, n (%)
< 5 | 62 (74%) | 58 (68%)
≥ 5 | 21 (25%) | 27 (32%)
Missing | 1 (1%) | 0

The percentages for subgroups of race and genotype do not add up to 100% due to rounding to 1 decimal place. The results of the efficacy analysis did not confirm the statistical superiority of ADAKVEO over placebo in reducing VOCs leading to a healthcare visit over the first-year post randomization.

Table 6: Efficacy Results From STAND Trial in Sickle Cell Disease
 |  |  |  | Between-Treatment Comparison
Treatment | n | Adjusted Annualized Rate of VOC | (95% CI) | Comparison | Rates Ratio | (95% CI)
ADAKVEO 5 mg/kg | 84 | 2.49 | (1.90, 3.26) | vs Placebo | 1.08 | (0.76, 1.55)*
Placebo | 85 | 2.30 | (1.75, 3.01)
n: Total number of participants included in the analysis.
Obtained from fitting a negative binomial regression model with treatment and randomization stratification factors (baseline VOC and HU/HC) as covariates. The natural log of the observation period was used as offset.
*The 95% CI includes 1, which indicates that the result is not statistically significant.

16 HOW SUPPLIED/STORAGE AND HANDLING

How Supplied

ADAKVEO (crizanlizumab-tmca) injection is a sterile, clear to opalescent, colorless to slightly brownish-yellow solution for intravenous infusion supplied as:

Carton containing one 100 mg/10 mL (10 mg/mL) single-dose vial NDC 0078-0883-61

The single-dose vial has a rubber stopper and an aluminum cap with a plastic flip-off disk. Each 10 mL vial is made of Type 1 glass.

Storage and Handling

- Store and transport refrigerated at 2°C to 8°C (36°F to 46°F) in the original carton to protect from light.
- Do not shake. Do not freeze.

17 PATIENT COUNSELING INFORMATION

Advise the patient to read the FDA-approved patient labeling (Patient Information).

Infusion-Related Reactions

Advise patients to contact their healthcare provider immediately for signs or symptoms of infusion-related reactions [see Warnings and Precautions (5.1)].

Interference With Automated Platelet Counts

Advise patients to inform their healthcare provider that they are receiving ADAKVEO prior to any blood tests due to the potential interference with laboratory tests used to measure platelet counts [see Warnings and Precautions (5.2)].

Manufactured by:
Novartis Pharmaceuticals Corporation
One Health Plaza
East Hanover, New Jersey 07936

US License No. 1244

© Novartis

T2024-48

PATIENT INFORMATION

ADAKVEO® (ah dak vee oh)
(crizanlizumab-tmca)
injection, for intravenous use

What is the most important information I should know about ADAKVEO?
ADAKVEO may cause serious side effects, including:

- Infusion-related reactions. Infusion-related reactions may happen during or within 24 hours of receiving an infusion of ADAKVEO. Infusion-related reactions may cause pain in different areas of your body. Your healthcare provider may slow down, temporarily stop, or completely stop your infusion with ADAKVEO if you have an infusion-related reaction. You may continue to receive ADAKVEO at a slower infusion rate and your healthcare provider may give you certain medicines before your infusion to lower your risk of getting an infusion-related reaction. Your healthcare provider should monitor you for signs and symptoms of infusion-related reactions and treat your symptoms as needed.
  Tell your healthcare provider right away if you get any of the following signs or symptoms of an infusion-related reaction:

- pain in different areas of your body
- headache
- fever
- chills or shivering
- nausea
- vomiting
- diarrhea

- tiredness
- dizziness
- sweating
- hives
- itching
- shortness of breath or wheezing

- ADAKVEO may interfere with a certain blood test. Tell your healthcare providers that you are receiving ADAKVEO before having any blood tests. ADAKVEO may interfere with a laboratory test to measure your platelet counts.

See "What are possible side effects of ADAKVEO?" for more information about side effects.

What is ADAKVEO?
ADAKVEO is a prescription medicine used in people 16 years of age and older who have sickle cell disease to help reduce how often painful crises happen.
It is not known if ADAKVEO is safe and effective in children under 16 years of age.

Before receiving ADAKVEO, tell your healthcare provider about all of your medical conditions, including if you:

- are pregnant or plan to become pregnant. ADAKVEO may harm your unborn baby. Talk to your healthcare provider about the possible risk to your unborn baby if you take ADAKVEO during pregnancy.
- are breastfeeding or plan to breastfeed. It is not known if ADAKVEO passes into your breast milk. You and your healthcare provider should decide the best way to feed your baby during treatment with ADAKVEO.

Tell your healthcare provider about all of the medicines you take, including prescription and over-the-counter medicines, vitamins, and herbal supplements.

How will I receive ADAKVEO?

- Your healthcare provider will give you ADAKVEO as an infusion into your vein through an intravenous (IV) line over 30 minutes.
- You will receive your first infusion, and then a second infusion 2 weeks later. After that, you will receive an infusion every 4 weeks.
- Your healthcare provider may also prescribe other treatments for you to take during treatment with ADAKVEO.
- Do not stop receiving ADAKVEO unless your healthcare provider tells you to.
- If you miss an appointment for infusion, call your healthcare provider as soon as possible to reschedule.

What are the possible side effects of ADAKVEO?
ADAKVEO may cause serious side effects.

- See "What is the most important information I should know about ADAKVEO?"

The most common side effects of ADAKVEO include:

- headache
- joint pain
- nausea
- back pain
- fatigue

- stomach pain
- fever
- diarrhea
- vomiting
- throat pain

These are not all of the possible side effects of ADAKVEO. For more information, ask your healthcare provider or pharmacist.
Call your doctor for medical advice about side effects. You may report side effects to FDA at 1-800-FDA-1088.

General information about the safe and effective use of ADAKVEO.

Medicines are sometimes prescribed for purposes other than those listed in a Patient Information leaflet. You can ask your pharmacist or healthcare provider for information about ADAKVEO that is written for health professionals.

What are the ingredients in ADAKVEO?

Active ingredient: crizanlizumab-tmca
Inactive ingredients: citric acid, polysorbate 80, sodium citrate, sucrose, and water for injection

Manufactured by: Novartis Pharmaceuticals Corporation, One Health Plaza, East Hanover, New Jersey 07936
U.S. License No. 1244
© Novartis
For more information, go to www.us.adakveo.com or call 1-888-NOWNOVA (1-888-669-6682).

This Patient Information has been approved by the U.S. Food and Drug Administration.

Revised: 6/2024

T2024-49

PRINCIPAL DISPLAY PANEL

NDC 0078-0883-61

Rx Only

ADAKVEO®

(crizanlizumab-tmca)
Injection

100 mg/10 mL
(10 mg/mL)

For intravenous infusion after dilution.

1 Single-Dose Vial.
Discard Unused Portion.

NOVARTIS